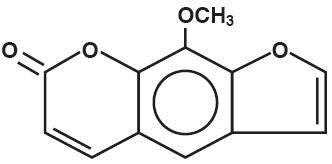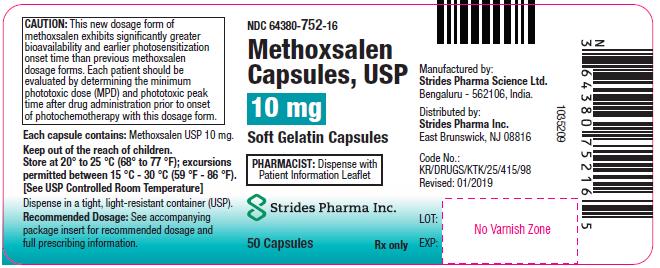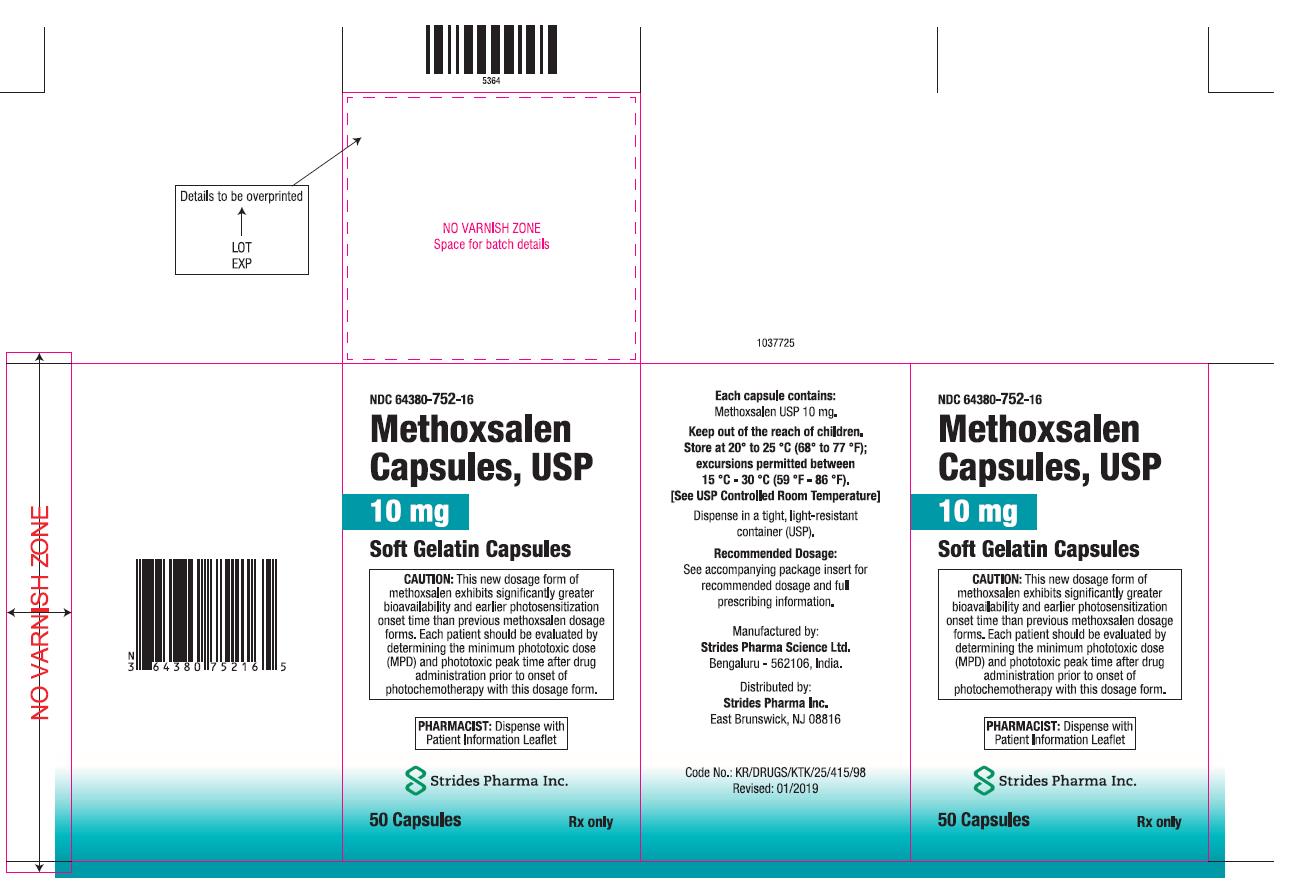 DRUG LABEL: Methoxsalen
NDC: 64380-752 | Form: CAPSULE, LIQUID FILLED
Manufacturer: Strides Pharma Science Limited
Category: prescription | Type: HUMAN PRESCRIPTION DRUG LABEL
Date: 20250311

ACTIVE INGREDIENTS: METHOXSALEN 10 mg/1 1
INACTIVE INGREDIENTS: GELATIN; GLYCERIN; GLYCINE; TITANIUM DIOXIDE; FD&C BLUE NO. 1; POLYETHYLENE GLYCOL 400; POLYSORBATE 80; MEDIUM-CHAIN TRIGLYCERIDES; ISOPROPYL ALCOHOL; D&C YELLOW NO. 10; ANHYDROUS CITRIC ACID; PROPYLENE GLYCOL; SHELLAC; BUTYL ALCOHOL; FERROSOFERRIC OXIDE; AMMONIA; WATER

Methoxsalen Capsules, USP 10 mg [Soft Gelatin Capsules]

Rx ONLY

CAUTION: METHOXSALEN IS A POTENT DRUG. READ ENTIRE BROCHURE PRIOR TO PRESCRIBING OR DISPENSING THIS MEDICATION.

BOXED WARNING

Methoxsalen with ultraviolet (UV) radiation should be used only by physicians who have special competence in the diagnosis and treatment of psoriasis and who have special training and experience in photochemotherapy. The use of Psoralen and ultraviolet radiation therapy should be under constant supervision of such a physician. For the treatment of patients with psoriasis, photochemotherapy should be restricted to patients with severe, recalcitrant, disabling psoriasis which is not adequately responsive to other forms of therapy, and only when the diagnosis is certain. Because of the possibilities of ocular damage, aging of the skin, and skin cancer (including melanoma), the patient should be fully informed by the physician of the risks inherent in this therapy.

BOXED WARNING

CAUTION: Methoxsalen Capsules, USP 10 mg [Soft Gelatin Capsules]. This new dosage form of methoxsalen exhibits significantly greater bioavailability and earlier photosensitization onset time than previous methoxsalen dosage forms. Patient should be treated in accordance with the dosimetry specifically recommended for this product. The minimum phototoxic dose (MPD) and phototoxic peak time after drug administration prior to onset of photochemotherapy with this dosage form should be determined.

I. DESCRIPTION

Methoxsalen Soft Gelatin Capsules USP contains 10mg methoxsalen. Methoxsalen occurs as white to pale yellow crystals and can be obtained naturally from seeds of Ammi majus and roots of Heracleum Candicans or through synthesis. Methoxsalen is practically insoluble in water, freely soluble in chloroform, soluble in boiling alcohol, in acetone, in acetic acid, in propylene glycol, and in benzene, sparingly soluble in boiling water and in ether. The chemical name of methoxsalen is 9-methoxy-7H-furo [3,2-g] [1] benzopyran-7-one; its empirical formula is C12H8O4 and the molecular weight is 216.19. The structural formula is:

Methoxsalen Capsules are available as soft gelatin capsules containing the following inactive ingredients: Citric acid anhydrous, D & C yellow 10, FD & C blue 1, Gelatin, Glycine, Glycerin, Isopropyl alcohol, Medium chain triglyceride, Polyethylene glycol 400, Polysorbate 80, Purified water, Titanium dioxide and Opacode black.

The opacode black contains Propylene glycol, Shellac glaze (Modified) IN SD-45, N-Butyl alcohol, Black iron oxide, Isopropyl alcohol and Ammonium hydroxide.

II. CLINICAL PHARMACOLOGY

The combination treatment regimen of psoralen (P) and ultraviolet radiation of 320-400 nm wavelength commonly referred to as UVA is known by the acronym, PUVA. Skin reactivity to UVA (320–400 nm) radiation is markedly enhanced by the ingestion of methoxsalen. In a well controlled bioavailability study, Methoxsalen Capsules, USP 10 mg [Soft Gelatin Capsules] reached peak drug levels in the blood of test subjects between 0.5 and 4 hours (Mean = 1.8 hours) as compared to between 1.5 and 6 hours (Mean = 3.0 hours) for regular hard gelatin capsule when administered with 8 ounces of milk. Peak drug levels were 2 to 3-fold greater when the overall extent of drug absorption was approximately 2-fold greater for Methoxsalen Capsules, USP 10 mg [Soft Gelatin Capsules] as compared to regular hard gelatin capsules. Detectable methoxsalen levels were observed up to 12 hours post dose. The drug half-life is approximately 2 hours. Photosensitivity studies demonstrate a shorter time of peak photosensitivity of 1.5 to 2.1 hours vs. 3.9 to 4.25 hours for regular hard gelatin capsules. In addition, the mean minimal erythema dose (MED), J/cm^2, for the Methoxsalen Capsules, USP 10 mg [Soft Gelatin Capsules] is substantially less than that required for regular hard gelatin capsule (Levins et al., 1984 and private communication^1).

Methoxsalen is reversibly bound to serum albumin and is also preferentially taken up by epidermal cells (Artuc et al., 1979^2). At a dose which is 6 times larger than that used in humans, it induces mixed function oxidases in the liver of mice (Mandula et al., 1978^3). In both mice and man, methoxsalen is rapidly metabolized. Approximately 95% of the drug is excreted as a series of metabolites in the urine within 24 hours (Pathak et al., 1977^4). The exact mechanism of action of methoxsalen with the epidermal melanocytes and keratinocytes is not known. The best known biochemical reaction of methoxsalen is with DNA. Methoxsalen, upon photoactivation, conjugates and forms covalent bonds with DNA which leads to the formation of both monofunctional (addition to a single strand of DNA) and bifunctional (crosslinking of psoralen to both strands of DNA) adducts (Dall' Acqua et al., 1971^5; Cole, 1970^6; Musajo et al., 1974^7; Dall' Acqua et al., 1979^8). Reactions with proteins have also been described (Yoshikawa, et al., 1979^9).

Methoxsalen acts as a photosensitizer. Administration of the drug and subsequent exposure to UVA can lead to cell injury. Orally administered methoxsalen reaches the skin via the blood and UVA penetrates well into the skin. If sufficient cell injury occurs in the skin, an inflammatory reaction occurs. The most obvious manifestation of this reaction is delayed erythema, which may not begin for several hours and peaks at 48-72 hours. The inflammation is followed, over several days to weeks, by repair which is manifested by increased melanization of the epidermis and thickening of the stratum corneum. The mechanisms of therapy are not known. In the treatment of psoriasis, the mechanism is most often assumed to be DNA photodamage and resulting decrease in cell proliferation but other vascular, leukocyte, or cell regulatory mechanisms may also be playing some role. Psoriasis is a hyperproliferative disorder and other agents known to be therapeutic for psoriasis are known to inhibit DNA synthesis.

III. INDICATIONS AND USAGE

Photochemotherapy (Methoxsalen with long wave UVA radiation) is indicated for the symptomatic control of severe, recalcitrant, disabling psoriasis not adequately responsive to other forms of therapy and when the diagnosis has been supported by biopsy. Methoxsalen is intended to be administered only in conjunction with a schedule of controlled doses of long wave ultraviolet radiation.

IV. CONTRAINDICATIONS

A. Patients exhibiting idiosyncratic reactions to psoralen compounds.

B. Patients possessing a specific history of light sensitive disease states should not initiate methoxsalen therapy except under special circumstances. Diseases associated with photosensitivity include lupus erythematosus, porphyria cutanea tarda, erythropoietic protoporphyria, variegate porphyria, xeroderma pigmentosum, and albinism.

C. Patients with melanoma or with a history of melanoma.

D. Patients with invasive squamous cell carcinomas.

E. Patients with aphakia, because of the significantly increased risk of retinal damage due to the absence of lenses.

V. WARNINGS - GENERAL

A. SKIN BURNING:

Serious burns from either UVA or sunlight (even through window glass) can result if the recommended dosage of the drug and/or exposure schedules are exceeded.

B. CARCINOGENICITY:

ANIMAL STUDIES: Topical or intraperitoneal methoxsalen has been reported to be a potent photocarcinogen in albino mice and hairless mice (Hakim et al., 1960^10). However, methoxsalen given by the oral route to Swiss albino mice suggests this agent exerts a protective effect against ultraviolet carcinogenesis; mice given 8-methoxypsoralen in their diet showed 38% ear tumors 180 days after the start of ultraviolet therapy compared to 62% for controls (O'Neal et al., 1957^11).

HUMAN STUDIES: A 5.7 year prospective study of 1380 psoriasis patients treated with oral methoxsalen and ultraviolet A photochemotherapy (PUVA) demonstrated that the risk of cutaneous squamous-cell carcinoma developing at least 22 months following the first PUVA exposure was approximately 12.8 times higher in the high dose patients than in the low dose patients (Stern et al., 1979^12, Stern et al., 1980^13, and Stern et al., 1984^14). The substantial dose-dependent increase was observed in patients with neither a prior history of skin cancer nor significant exposure to cutaneous carcinogens. Reduction in PUVA dosage significantly reduces the risk. No substantial dose-related increase was noted for basal cell carcinoma according to Stern et al., 1984^14. Increases appear greatest in patients who have pre-PUVA exposure to 1) prolonged tar and UVB treatment, 2) ionizing radiation, or 3) arsenic. Roenigk et al., 1980^15, studied 690 patients for up to 4 years and found no increase in the risk of non-melanoma skin cancer, although patients in this cohort had significantly less exposure to PUVA than in the Stern et al. study. Recent analysis of new data in the Stern et al cohort (Stern et al., 1997^16) has shown that these patients have an elevated relative risk of contracting melanoma. The relative risk for melanoma in these patients was 2.3 (95% confidence interval 1.1 to 4.1). The risk is particularly higher in those patients who have received more than 250 PUVA treatments and in those whose treatment has spanned greater than 15 years earlier. Some patients developing melanoma did so even after having ceased PUVA therapy over 5 years earlier. These observations indicate the need for monitoring of PUVA patients for skin tumors throughout their lives. In a study in Indian patients treated for 4 years for vitiligo, 12% developed keratoses, but not cancer, in the depigmented, vitiliginous areas (Mosher, 1980^17). Clinically, the keratoses were keratotic papules, actinic keratosis-like macules, nonscaling dome-shaped papules, and lichenoid porokeratotic-like papules.

C. CATARACTOGENICITY:

ANIMAL STUDIES: Exposure to large doses of UVA causes cataracts in animals, and this effect is enhanced by the administration of methoxsalen (Cloud et al., 1960^18; Cloud et al., 1961^19 Freeman et al., 1969^20).

HUMAN STUDIES: It has been found that the concentration of methoxsalen in the lens is proportional to the serum level. If the lens is exposed to UVA during the time methoxsalen is present in the lens, photochemical action may lead to irreversible binding of methoxsalen to proteins and the DNA components of the lens (Lerman et al., 1980^21). However, if the lens is shielded from UVA, the methoxsalen will diffuse out of the lens in a 24-hour period (Lerman et al., 1980^21). Patients should be told emphatically to wear UVA absorbing, wrap-around sunglasses for the 24-hour period following ingestion of methoxsalen whether exposed to direct or indirect sunlight in the open or through a window glass. Among patients using proper eye protection, there is no evidence for a significantly increased risk of cataracts in association with PUVA therapy (Stern et al., 1979^12). Thirty-five of 1380 patients have developed cataracts in the 5 years since their first PUVA treatment. This incidence is comparable to that expected in a population of this size and age distribution. No relationship between PUVA dose and cataract risk in this group has been noted.

D. ACTINIC DEGENERATION:

Exposure to sunlight and/or ultraviolet radiation may result in "premature aging" of the skin.

E. BASAL CELL CARCINOMAS:

Patients exhibiting multiple basal cell carcinomas or having a history of basal cell carcinomas should be diligently observed and treated.

F. RADIATION THERAPY:

Patients having a history of previous x-ray therapy or grenz ray therapy should be diligently observed for signs of carcinoma.

G. ARSENIC THERAPY:

Patients having a history of previous arsenic therapy should be diligently observed for signs of carcinoma.

H. HEPATIC DISEASES:

Patients with hepatic insufficiency should be treated with caution since hepatic biotransformation is necessary for drug urinary excretion.

I. CARDIAC DISEASES:

Patients with cardiac diseases or others who may be unable to tolerate prolonged standing or exposure to heat stress should not be treated in a vertical UVA chamber.

J. GERIATRIC PATIENTS:

Caution should be used in elderly patients, especially those with a pre-existing history of cataracts, cardiovascular conditions, kidney and/or liver dysfunction, or skin cancer.

K. TOTAL DOSAGE:

The total cumulative dose of UVA that can be given over long periods of time with safety has not as yet been established.

L. CONCOMITANT THERAPY:

Special care should be exercised in treating patients who are receiving concomitant therapy (either topically or systemically) with known photosensitizing agents such as anthralin, coal tar or coal tar derivatives, griseofulvin, phenothiazines, nalidixic acid, fluoroquinolone antibiotics, halogenated salicylanilides (bacteriostatic soaps), sulfonamides, tetracyclines, thiazides and certain organic staining dyes such as methylene blue, toluidine blue, rose bengal, and methyl orange.

VI. PRECAUTIONS

A. GENERAL - APPLICABLE TO PSORIASIS TREATMENT:

BEFORE METHOXSALEN INGESTION

Patients must not sunbathe during the 24 hours prior to methoxsalen ingestion and UV exposure. The presence of a sunburn may prevent an accurate evaluation of the patient's response to photochemotherapy.

AFTER METHOXSALEN INGESTION

UVA-absorbing wrap-around sunglasses should be worn during daylight for 24 hours after methoxsalen ingestion. The protective eyewear must be designed to prevent entry of stray radiation to the eyes, including that which may enter from the sides of the eyewear. The protective eyewear is used to prevent the irreversible binding of methoxsalen to the proteins and DNA components of the lens. Cataracts form when enough of the binding occurs. Visual discrimination should be permitted by the eyewear of patient well-being and comfort.

Patients must avoid sun exposure, even through window glass or cloud cover, for at least 8 hours after methoxsalen ingestion. If sun exposure cannot be avoided, the patient should wear protective devices such as a hat and gloves, and/or apply sunscreens which contain ingredients that filter out UVA radiation (e.g., sunscreens containing benzophenone and/or PABA esters which exhibit a sun protective factor equal to or greater than 15). These chemical sunscreens should be applied to all areas that might be exposed to the sun (including lips). Sunscreens should not be applied to areas affected by psoriasis until after the patient has been treated in the UVA chamber.

DURING PUVA THERAPY

Total UVA-absorbing/blocking goggles mechanically designed to give maximal ocular protection must be worn. Failure to do so may increase the risk of cataract formation. A reliable radiometer can be used to verify elimination of UVA transmission through the goggles.

Abdominal skin, breasts, genitalia, and other sensitive areas should be protected for approximately 1/3 of the initial exposure time until tanning occurs.

Unless affected by disease, male genitalia should be shielded.

AFTER COMBINED METHOXSALEN/UVA THERAPY

UVA-absorbing wrap-around sunglasses should be worn during daylight for 24 hours after combined methoxsalen/UVA therapy.

Patients should not sunbathe for 48 hours after therapy. Erythema and/or burning due to photochemotherapy and sunburn due to sun exposure are additive.

B. INFORMATION FOR PATIENTS:

See accompanying Patient Package Insert.

C. LABORATORY TESTS:

Patients should have an ophthalmologic examination prior to start of therapy, and thence yearly.

Patients should have routine laboratory tests prior to the start of therapy and at regular periods thereafter if patients are on extended treatments.

D. DRUG INTERACTIONS:

See WARNINGS – GENERAL.

E. CARCINOGENESIS:

See WARNINGS – GENERAL.

F. PREGNANCY:

Animal reproduction studies have not been conducted with methoxsalen. It is also not known whether methoxsalen can cause fetal harm when administered to a pregnant woman or can affect reproduction capacity. Methoxsalen should be given to a woman with reproductive capacity only if clearly needed.

G. NURSING MOTHERS:

It is not known whether this drug is excreted in human milk. Because many drugs are excreted in human milk, either methoxsalen ingestion or nursing should be discontinued.

H. PEDIATRIC USE:

Safety in children has not been established. Potential hazards of long-term therapy include the possibilities of carcinogenicity and cataractogenicity as described in the WARNINGS - GENERAL section as well as the probability of actinic degeneration which is also described in the WARNINGS - GENERAL Section.

I. GERIATRIC USE:

Clinical studies with Methoxsalen Capsules, USP 10 mg [Soft Gelatin Capsules] did not include sufficient numbers of subjects aged 65 and over to determine whether elderly subjects responded differently from younger subjects. Other reported clinical experience has not identified differences in response between the elderly and younger patients. In general, dose selection for an elderly patient should be cautious, usually starting at the low end of the dosing range, reflecting the greater frequency of decreased hepatic, renal, or cardiac function, and of concomitant disease or other drug therapy.

VII. ADVERSE REACTIONS:

A. METHOXSALEN:

The most commonly reported side effect of methoxsalen alone is nausea, which occurs with approximately 10% of all patients. This effect may be minimized or avoided by instructing the patient to take methoxsalen in milk or food, or to divide the dose into two portions, taken approximately one-half hour apart. Other effects include nervousness, insomnia, and depression.

B. COMBINED METHOXSALEN/UVA THERAPY:

PRURITUS: This adverse reaction occurs with approximately 10% of all patients. In most cases, pruritus can be alleviated with frequent application of bland emollients or other topical agents; severe pruritus may require systemic treatment. If pruritus is unresponsive to these measures, shield pruritic areas from further UVA exposure until the condition resolves. If intractable pruritus is generalized, UVA treatment should be discontinued until the pruritus disappears.

ERYTHEMA: Mild, transient erythema at 24-48 hours after PUVA therapy is an expected reaction and indicates that a therapeutic interaction between methoxsalen and UVA occurred. Any area showing moderate erythema (greater than Grade 2 - See Table 1 for grades of erythema) should be shielded during subsequent UVA exposures until the erythema has resolved. Erythema greater than Grade 2 which appears within 24 hours after UVA treatment may signal a potentially severe burn. Erythema may become progressively worse over the next 24 hours, since the peak erythemal reaction characteristically occurs 48 hours or later after methoxsalen ingestion. The patient should be protected from further UVA exposures and sunlight, and should be monitored closely.

IMPORTANT DIFFERENCES BETWEEN PUVA ERYTHEMA AND SUNBURN: PUVA-induced inflammation differs from sunburn or UVB phototherapy in several ways. The % transmission of UVB varies between 0% to 34% through skin whereas UVA varies between 1% to 80% transmission; thus, UVA is transmitted to a larger % through the skin. (Diffey, 1982^22). The DNA lesions induced by PUVA are very different from UV-induced thymine dimers and may lead to a DNA crosslink. This DNA lesion may be more problematic to the cell because crosslinks are more lethal and psoralen-DNA photoproducts may be "new" or unfamiliar substrates for DNA repair enzymes. DNA synthesis is also suppressed longer after PUVA. The time course of delayed erythema is different with PUVA and may not involve the usual mediators seen in sunburn. PUVA-induced redness may be just beginning at 24 hours, when UVB erythema has already passed its peak. The erythema dose-response curve is also steeper for PUVA. Compared to equally erythemogenic doses of UVB, the histologic alterations induced by PUVA show more dermal vessel damage and longer duration of epidermal and dermal abnormalities.

OTHER ADVERSE REACTIONS: Those reported include edema, dizziness, headache, malaise, depression, hypopigmentation, vesiculation and bullae formation, non-specific rash, herpes simplex, miliaria, urticaria, folliculitis, gastrointestinal disturbances, cutaneous tenderness, leg cramps, hypotension, and extension of psoriasis.

To report SUSPECTED ADVERSE REACTION, contact Strides Pharma Inc. at 1-877-244-9825 or go to www.strides.com or FDA at 1-800-FDA-1088 or www.fda.gov/medwatch.

VIII. OVERDOSAGE

In the event of methoxsalen overdosage, induce emesis and keep the patient in a darkened room for at least 24 hours. Emesis is most beneficial within the first 2 to 3 hours after ingestion of methoxsalen, since maximum blood levels are reached by this time.

IX. DRUG DOSAGE & ADMINISTRATION

CAUTION: Methoxsalen Capsules, USP represents a new dose form of methoxsalen. This new dosage form of methoxsalen exhibits significantly greater bioavailability and earlier photosensitization onset time than previous methoxsalen dosage forms. Each patient should be evaluated by determining the minimum phototoxic dose (MPD) and phototoxic peak time after drug administration prior to onset of photochemotherapy with this dosage form. Human bioavailability studies have indicated the following drug dosage and administration directions are to be used as a guideline only.

PSORIASIS THERAPY

1. DRUG DOSAGE -INITIAL THERAPY: Methoxsalen capsules should be taken 1-1/2 to 2 hours before UVA exposure with some low-fat food or milk according to the following table:

Patient's Weight
Dose
(kg) | (lbs) | (mg)
<30 | <66 | 10
30-50 | 66-110 | 20
51-65 | 112-143 | 30
66-80 | 146-176 | 40
81-90 | 179-198 | 50
91-115 | 201-254 | 60
>115 | >254 | 70

Geriatric patients should generally be started at the low end of the dose recommended according to body weight and closely monitored during PUVA therapy. Although clinical experience has not identified differences in response between elderly and younger patients, the use of methoxsalen in older individuals may be affected by the presence of pre-existing medical conditions.

2. INITIAL EXPOSURE: The initial UVA exposure energy level and corresponding time of exposure is determined by the patient's skin characteristics for sun burning and tanning as follows:

Skin Type | History | Recommended J/cm^2
I | Always burn, never tan (patients with erythrodermic psoriasis are to be classed as Type I for determination of UVA dosage.) | 0.5 J/cm^2
II | Always burn, but sometimes tan | 1.0 J/cm^2
III | Sometimes burn, but always tan | 1.5 J/cm^2
IV | Never burn, always tan | 2.0 J/cm^2
Skin Type | Physician Examination | J/cm^2
V* | Moderately pigmented | 2.5 J/cm^2
VI* | Blacks | 3.0 J/cm^2
*Patients with natural pigmentation of these types should be classified into a lower skin type category if the sunburning history so indicates.

If the MPD is done, start at 1/2 MPD.

Additional drug dosage directions are as follows:

Weight Change: In the event that the weight of a patient changes during treatment such that he/she falls into an adjacent weight range/dose category, no change in the dose of methoxsalen is usually required. If, in the physician's opinion, however, a weight change is sufficiently great to modify the drug dose, then an adjustment in the time of exposure to UVA should be made.

Dose/Week: The number of doses per week of methoxsalen capsules will be determined by the patient's schedule of UVA exposures. In no case should treatments be given more often than once every other day because the full extent of phototoxic reactions may not be evident until 48 hours after each exposure.

Dosage Increase: Dosage may be increased by 10 mg. after the 15th treatment under the conditions outlined in section XI.B.4.b.

A. IRRADIANCE UNIFORMITY

The following specifications should be met with the window of the detector held in a vertical plane:

Vertical Variation: For readings taken at any point along the vertical center axis of the chamber (to within 15 cm from the top and bottom), the lowest reading should not be less than 70 % of the highest reading.

Horizontal Variation: Throughout any specific horizontal plane, the lowest reading must be at least 80 % of the highest reading, excluding the peripheral 3 cm of the patient treatment space.

B. PATIENT SAFETY FEATURES:

The following safety features should be present: (1) Protection from electrical hazard: All units should be grounded and conform to applicable electrical codes. The patient or operator should not be able to touch any live electrical parts. There should be ground fault protection. (2) Protective shielding of lamps: The patient should not be able to come in contact with the bare lamps. In the event of lamp breakage, the patient should not be exposed to broken lamp components. (3) Hand rails and hand holds: Appropriate supports should be available to the patient. (4) Patient viewing window: A window which blocks UV should be provided for viewing the patient during treatment. (5) Door and latches: Patients should be able to open the door from the inside with only slight pressure to the door. (6) Non-skid floor: The floor should be of a non-skid nature. (7) Thermoregulation: Sufficient air flow should be provided for patient safety and comfort, limiting temperature within the UVA radiator cabinet to approximately less than 100 °F. (8) Timer: The irradiator should be equipped with an automatic timer which terminates the exposure at the conclusion of a pre-set time interval. (9) Patient alarm device: An alarm device within the UVA irradiator chamber should be accessible to the patient for emergency activation. (10) Danger label: The unit should have a label prominently displayed which reads as follows:

DANGER - Ultraviolet radiation - Follow your physicians instructions - Failure to use protective eyewear may result in eye injury.

C. UVA EXPOSURE DOSIMETRY MEASUREMENTS:

The maximum radiant exposure or irradiance (within ±15%) of UVA (320-400 nm) delivered to the patient should be determined by using an appropriate radiometer calibrated to be read in J/cm^2 or mW/cm^2. In the absence of a standard measuring technique approved by the National Bureau of Standards, the system should use a detector corrected to a cosine spatial response. The use and recalibration frequency of such a radiometer for a specific UVA irradiator chamber should be specified by the manufacturer because the UVA dose (exposure) is determined by the design of the irradiator, the number of lamps, and the age of the lamp. If irradiance is measured, the radiometer reading in mW/cm^2 is used to calculate the exposure time in minutes to deliver the required UVA in J/cm^2 to a patient in the UVA irradiator cabinet. The equation is:

Exposure Time Desired UVA Dose (J/cm^2)

(minutes) = -------------------------------------

0.06 x Irradiance (mW/cm^2)

Overexposure due to human error should be minimized by using an accurate automatic timing device, which is set by the operator and controlled by energizing and de-energizing the UVA irradiator lamp. The timing device calibration interval should be specified by the manufacturer. Safety systems should be included to minimize the possibility of delivering a UVA exposure which exceeds the prescribed dose, in the event the timer or radiometer should malfunction.

D. UVA SPECTRAL OUTPUT DISTRIBUTION:

The spectral distributions of the lamps should meet the following specifications:

Wavelength band (nanometers) | Output^1
<310 ……………. | <1
310 to 320 ……………. | 1 to 3
320 to 330 ……………. | 4 to 8
330 to 340 ……………. | 11 to 17
340 to 350 ……………. | 18 to 25
350 to 360 ……………. | 19 to 28
360 to 370 ……………. | 15 to 23
370 to 380 ……………. | 8 to 12
380 to 390 ……………. | 3 to 7
390 to 400 ……………. | 1 to 3
^1As a percentage of total irradiance between 320 and 400 nanometers.

INTRODUCTION:

The Methoxsalen Capsules, USP 10 mg [Soft Gelatin Capsules] reach their maximum bioavailability in 1-1/2 to 2 hours after ingestion.

On average, the serum level achieved with Methoxsalen Capsules, USP 10 mg [Soft Gelatin Capsules] is twice that obtained with hard gelatin capsules and reach their peak concentration in less than half the time of the hard gelatin capsules.

As a result the mean MED J/cm^2 for the Methoxsalen Capsules, USP 10 mg [Soft Gelatin Capsules] is substantially less than that required for hard gelatin capsules (Levins et al., 1984 and private communication^1).

Photosensitivity studies demonstrate a shorter time of peak photosensitivity of 1.5 to 2.1 hours vs. 3.9 to 4.25 hours for regular methoxsalen capsules.

A. INITIAL EXPOSURE:

The initial UVA exposures should be conducted according to the guidelines presented previously under IX. Psoriasis therapy, Drug dosage-initial Therapy and initial Exposure.

B. CLEARING PHASE:

Specific recommendations for patient treatment are as follows:

SKIN TYPES I, II, & III. Patients with skin types I, II, and III may be treated 2 or 3 times per week. UVA exposure may be held constant or increased by up to 1.0 J/cm^2 at each treatment, according to the patient's response. If erythema occurs, however, do not increase exposure time until erythema resolves. The severity and extent of the patient's erythema may be used to determine whether the next exposure should be shortened, omitted, or maintained at the previous dosage. (See ADVERSE REACTIONS.)

SKIN TYPES IV, V, & VI. Patients with skin types IV, V, and VI may be treated 2 or 3 times per week. UVA exposure may be held constant or increased by up to 1.5 J/cm^2 at each treatment unless erythema occurs. If erythema occurs, follow instructions outlined above in the procedures for patients with skin types I, II, and III.

ERYTHRODERMIC PSORIASIS. Patients with erythrodermic psoriasis should be treated with special attention because pre-existing erythema may obscure observations of possible treatment-related phototoxic erythema. These patients may be treated 2 or 3 times per week, as a Type I patient.

MISCELLANEOUS SITUATIONS:

If there is no response after a total of 10 treatments, the exposure of UVA energy may be increased by an additional 0.5–1.0 J/cm^2 above the prior incremental increases for each treatment. (Example: a patient whose exposure dosage is being increased by 1.0 J/cm^2 may now have all subsequent doses increased by 1.5–2.0 J/cm^2.)

If there is no response, or only minimal response, after 15 treatments, the dosage of methoxsalen may be increased by 10 mg (a one-time increase in dosage). This increased dosage may be continued for the remainder of the course of treatment but should not be exceeded.

If a patient misses a treatment, the UVA exposure time of the next treatment should not be increased. If more than one treatment is missed, reduce the exposure by 0.5 J/cm^2 for each treatment missed.

If the lower extremities are not responding as well as the rest of the body and do not show erythema, cover all other body areas and give 25 % of the present exposure dose as an additional exposure to the lower extremities. This additional exposure to the lower extremities should be terminated if erythema develops on these areas.

Non-responsive psoriasis: If a patient's generalized psoriasis is not responding, or if the condition appears to be worsening during treatment, the possibility of a generalized phototoxic reaction should be considered. This may be confirmed by the improvement of the condition following temporary discontinuance of this therapy for two weeks. If no improvement occurs during the interruption of treatment, this patient may be considered a treatment failure.

C. ALTERNATIVE EXPOSURE SCHEDULE:

As an alternative to increasing the UVA exposure at each treatment, the following schedule may be followed; this schedule may reduce the total number of J/cm^2 received by the patient over the entire course of therapy.

Incremental increases in UVA exposure for all patients may range from 0.5 to 1.5 J/cm^2, according to the patient's response to therapy.

Once Grade 2 clearing (see Table 2) has been reached and the patient is progressing adequately, UVA dosage is held constant. This dosage is maintained until Grade 4 clearing is reached.

If the rate of clearing significantly decreases, exposure dosage may be increased at each treatment (0.1-1.5 J/cm^2) until Grade 3 clearing and a satisfactory progress rate is attained. The UVA exposure will be held constant again until Grade 4 clearing is attained. These increases may be used also if the rate of clearing significantly decreases between Grade 3 and Grade 4 response. However, the possibility of a phototoxic reaction should be considered; see Non-responsive Psoriasis, above.

In summary, this schedule raises slightly the increments (J/cm^2) of UVA dosage, but limits these increases to those periods when the patient is not responding adequately. Otherwise, the UVA exposure is held at the lowest effective dose.

D. MAINTENANCE PHASE:

The goal of maintenance treatment is to keep the patient as symptom-free as possible with the least amount of UVA exposure.

SCHEDULE OF EXPOSURES: When patients have achieved 95% clearing, or Grade 4 response (Table 2), they may be placed on the following maintenance schedules (M1 – M4), in sequence. It is recommended that each maintenance schedule be adhered to for at least 2 treatments (unless erythema or psoriatic flare occurs, in which case see (2a) and (2b) below).

Maintenance Schedules

M1 - once/week

M2 - once/2 weeks

M3 - once/3 weeks

M4 - p.r.n. (i.e., for flares)

LENGTH OF EXPOSURE: The UVA exposure for the first maintenance treatment of any schedule (except M4 as noted below) is the same as that of the patient's last treatment under the previous schedule. For skin types I–IV, however, it is recommended that the maximum UVA dosage during maintenance treatments not exceed the following:

Skin Types | J/cm^2/treatment
I | 12
II | 14
III | 18
IV | 22

If the patient develops erythema or new lesions of psoriasis, proceed as follows: a. Erythema: During maintenance therapy, the patient's tan and threshold dose for erythema may gradually decrease. If maintenance treatments produce significant erythema, the exposure to UVA should be decreased by 25% until further treatments no longer produce erythema.

b. Psoriasis: If the patient develops new areas of psoriasis during maintenance therapy (but still is classified as having a Grade 4 response), the exposure to UVA may be increased by 0.5-1.5 J/cm^2 at each treatment; this is appropriate for all types of patients. These increases are continued until the psoriasis is brought under control and the patient is again clear. The exposure being administered when this clearing is reached should be used for further maintenance treatment.

FLARES DURING MAINTENANCE: If the patient flares during maintenance treatment (i.e., develops psoriasis on more than 5% of the originally involved areas of the body), this maintenance treatment schedule may be changed to the preceding maintenance or clearing schedule. The patient may be kept on his schedule until again 95 % clear. If the original maintenance treatment schedule is unable to control the psoriasis, the schedule may be changed to a more frequent regimen. If a flare occurs less than 6 weeks after the last treatment, 25 % of the maximum exposure received during the clearing phase, with the clearing schedule received during the clearing phase, may be used and then proceed with the clearing schedule previously followed for this patient. (At 95% clearing, follow regular maintenance until the optimum maintenance schedule is determined for the patient.) If more than 6 weeks have elapsed since the last treatment was given, treat patients as if they were beginning therapy insofar as exposure dosages are concerned, since their threshold for erythema may have decreased.

Table 1. Grades of Erythema
Grade | Erythema
0 | No erythema
1 | Minimally perceptible erythema - faint pink
2 | Marked erythema but with no edema
3 | Fiery erythema with edema
4 | Fiery erythema with edema and blistering

Table 2. Response To Therapy
Grade | Criteria | Percent Improvement
 |  | (compared to original
 |  | extent of disease)
-1 | Psoriasis worse……………………………………... | 0
0 | No change………………………………………….. | 0
1 | Minimal improvement - slightly less scale and/or erythema……………………………………………. | 5-20
2 | Definite improvement - partial flattening of all plaques-less scaling and less erythema…………….. | 20-50
3 | Considerable improvement - nearly complete flattening of all plaques but borders of plaques still palpable……………………………………………… | 50-95
4 | Clearing; complete flattening of plaques including borders; plaques may be outlined by pigmentation…. | 95

XII. HOW SUPPLIED

Methoxsalen Capsules, USP 10 mg is green color, oval shaped soft gelatin capsule imprinted with 'M10' containing no drug crystals and clear colorless to pale yellow liquid, each containing 10 mg of methoxsalen (8-methoxypsoralen). It is packed in amber colored glass bottles as 50's count (NDC 64380-752-16).

Store at 20° to 25 °C (68° to 77 °F); excursions permitted between 15 °C - 30 °C (59 °F - 86 °F).

[See USP Controlled Room Temperature]

Manufactured by:

Strides Pharma Science Ltd.

Bengaluru - 562106, India

Distributed by:

Strides Pharma Inc.

East Brunswick, NJ 08816

BIBLIOGRAPHY

1. Levins, P.C., Gange, R.W., Momtaz-T,K., Parrish, J.A., and Fitzpatrick, T.B.: A New Liquid Formulation of 8-Methoxypsoralen: Bioactivity and Effect of Diet: JID, 82, No. 2, pp. 185-187 (1984) and private communication.
2. Artuc, M., Stuettgen, G., Schalla, W., Schaefer, H., and Gazith, J.: Reversible binding of 5- and 8-methoxypsoralen to human serum proteins (albumin) and to epidermis in vitro: Brit. J. Dermat. 101, pp. 669-677 (1979).
3. Mandula, B.B., Pathak, M.A., Nakayama, T., and Davidson, S.J.: Induction of mixed-function oxidases in mouse liver by psoralens., Ibid, 99, pp. 687-692 (1978).
4. Pathak, M. A., Fitzpatrick, T. B., Parrish, J. A.: PSORIASIS, Proceedings of the Second International Symposium. Edited by E.M. Farber, A.J. Cox, Yorke Medical Books, pp. 262-265 (1977).
5. Dall'Acqua, F., Marciani, S., Ciavatta, L., Rodighiero, G.: Formation of interstrand cross-linkings in the photoreactions between furocoumarins and DNA; Z Naturforsch (B), 26, pp. 561-569 (1971).
6. Cole, R. S.: Light-induced cross-linkings of DNA in the presence of a furocoumarin (psoralen), Biochem. Biophys. Acta, 217, pp. 30-39 (1970).
7. Musajo, L., Rodighiero, G., Caporale, G., Dall'Acqua, F., Marciani, S., Bordin, F., Baccichetti, F., Bevilacqua, R.: Photoreactions between Skin-Photosensitizing Furocoumarins and Nucleic Acids, Sunlight and Man; Normal and Abnormal Photobiologic Responses. Edited by M. A. Pathak, L. C. Harber, M. Seiji et al. University of Tokyo Press, pp. 369-387 (1974).
8. Dall'Acqua, F., Vedaldi, D., Bordin, F., and Rodighiero, G.: New studies in the interaction between 8-methoxypsoralen and DNA in vitro; JID, 73, pp. 191-197 (1979).
9. Yoshikawa, K., Mori, N., Sakakibara, S., Mizuno, N., Song, P.: Photo Conjugation of 8-methoxypsoralen with Proteins; Photochem. & Photobiol. 29, pp. 1127-1133 (1979).
10. Hakim, R.D., Griffin, A.C.: Knox, J.M.: Erythema and tumor formation in methoxsalen treated mice exposed to fluorescent light; Arch. Dermatol. 82, pp. 572-577 (1960).
11. O'Neal, M.A., Griffin, A.C.: The Effect of Oxypsoralen upon Ultraviolet Carcinogenesis in Albino Mice, Cancer Res., 17, pp. 911-916 (1957).
12. Stern, R.S., Unpublished personal communication.
13. Stern, R.S., Parrish, J.A., Zierler, S.: Skin Carcinoma in Patients with Psoriasis Treated with Topical Tar and Artificial Ultraviolet Radiation. Lancet, 1, pp. 732-735 (1980).
14. Stern, R.S., Laird, N., Melski, J., Parrish, J.A., Fitzpatrick, T.B., Bleich, H.L.: Cutaneous Squamous-Cell Carcinoma in Patients Treated with PUVA: NEJM, 310, No. 18, pp. 1156-1161 (1984).
15. Roenigk, Jr., H.H., and 12 Cooperating Investigators: Skin Cancer in the PUVA-48 Cooperative Study of Psoriasis. Program for Forty-First Annual Meeting for The Society of Investigative Dermatology, Inc., Sheraton Washington Hotel, Washington, D.C., May 12, 13, and 14, 1980. Abstract JID, 74 No. 4, pp. 250 (April 1980).
16. Stern et al., Malignant melanoma in patients treated for psoriasis with methoxsalen (psoralen) and ultraviolet A radiation (PUVA). The PUVA Follow-Up Study. New England Journal of Medicine, 336:1041-1045, (April 10, 1997).
17. Mosher, D.B., Pathak, M.A., Harris, T.J., Fitzpatrick, T.B.: Development of Cutaneous Lesions in Vitiligo During Long-Term PUVA Therapy. Program for Forty-First Annual Meeting for The Society for Investigative Dermatology, Inc., Sheraton Washington Hotel, Washington, D.C., May 12, 13, and 14, 1980. Abstracts JID, 74, No. 4, p. 259 (April, 1980).
18. Cloud, T.M., Hakim, R., Griffin, A.C.: Photosensitization of the eye with methoxsalen. I. Acute effects; Arch. Ophthalmol. 64, pp. 346-352 (1960).
19. Cloud, T. M., Hakim, R., Griffin, A. C.: Photosensitization of the eye with methoxsalen. II. Chronic effects, Ibid, 66, pp. 689-694 (1961).
20. Freeman, R. G., Troll, D.: Photosensitization of the eye by 8-methoxypsoralen, JID, 53, pp. 449-453 (1969).
21. Lerman, S., Megaw, J., Willis, I.: Potential ocular complications from PUVA therapy and their prevention; JID 74, pp. 197-199 (1980).
22. Diffey, >L., Medical Physics Handbook 11, Ultraviolet Radiation In Medicine, Adam Hilger, Ltd., Bristol, p. 86 (1982)

Revised: 01/2019

MEDICATION GUIDE

PATIENT INFORMATION ON THE USE OF METHOXSALEN CAPSULES, USP 10 MG [SOFT GELATIN CAPSULES]

IN THE TREATMENT OF PSORIASIS

This brochure is intended to provide you with information about the treatment of psoriasis. The entire brochure should be read so that you are aware of the requirements on your part to ensure the effectiveness and safety of the therapy. Any additional questions that you may have can be answered by your doctor or pharmacist. In addition, the pharmacist will have a copy of a very technical brochure entitled the "Physician's Package Insert" that you may wish to read.

A. What Is Methoxsalen Capsules, USP 10 mg [Soft Gelatin Capsules]?

Methoxsalen Capsules, USP 10 mg [Soft Gelatin Capsules] is a drug which has been shown to be effective in the treatment of psoriasis when combined with exposure to a very specific kind of light. The use of the drug must be combined with exposure to the special light to produce effective therapy. Methoxsalen Capsules, USP 10 mg [Soft Gelatin Capsules] represents a new dose form of methoxsalen. This new dosage form of methoxsalen exhibits significantly greater bioavailability and earlier photosensitization onset time than previous methoxsalen dosage forms.

B. What Is The Special Light?

Light is classified into many different parts. One part is known as ultraviolet light, which is a normal component of sunlight. Artificial or man-made light sources are now available that produce the special part of light (ultraviolet "A") necessary for the most effective therapy.

C. What Is "PUVA"?

"PUVA" is the name of the treatment for psoriasis and stands for the use of Psoralen drug (Methoxsalen Capsules, USP 10 mg [Soft Gelatin Capsules]) in combination with UltraViolet A light.

D. What Is Psoriasis?

Psoriasis is a skin condition associated with red and scaly patches. The cause of psoriasis is not known. PUVA (Methoxsalen Capsules, USP 10 mg [Soft Gelatin Capsules] with ultraviolet A light) is used for the treatment of severe psoriasis that has not been helped by other methods of therapy.

E. What Should The Patient Do Before PUVA Therapy?

Certain other medicines can make you more sensitive to the combination drug and light treatment. In addition, certain other medical conditions can be aggravated by this treatment. Before starting treatment, be sure to tell your doctor if you have experienced any of the following:

1. had a severe reaction to Methoxsalen Capsules, USP 10 mg [Soft Gelatin Capsules] in the past
2. had recent x-ray treatment or planning any
3. have or ever have had skin cancer
4. have or ever have had any eye problems such as cataracts or loss of the lens of the eyes
5. have or ever have had liver problems
6. have or ever have had heart or blood pressure problems
7. have any medical condition that requires you to stay out of the sun such as lupus erythematosus
8. are taking any drugs (either prescription or nonprescription). Some drugs can increase your sensitivity to ultraviolet light either from the sun or man-made sources. Examples of such drugs include major tranquilizers, sulfa drugs for the treatment of infection or diabetes, tetracycline, antibiotics, griseofulvin products, thiazide-containing diuretics (blood pressure or water elimination drugs), and certain antibacterial or deodorant soaps

F. How Should The Patient Take Methoxsalen Capsules, USP 10 mg [Soft Gelatin Capsules]?

1. The number of capsules recommended by your doctor should be taken with some food or low fat milk two hours before ultraviolet light treatment.
2. Methoxsalen Capsules, USP 10 mg [Soft Gelatin Capsules] is a potent drug. Never take more than is prescribed for you since it may result in burning and/or blistering of your skin after exposure to ultraviolet light.

G. What Precautions Should Be Taken During And After PUVA Therapy?

1. Eye Protection — Make sure that you wear special wrap-around sunglasses that totally block or absorb ultraviolet light. Put them on immediately after taking Methoxsalen Capsules, USP 10 mg [Soft Gelatin] and continue wearing them for 24 hours if any light is present (even if indirect such as reflection or through window glass). Ordinary sunglasses are not adequate.
2. Skin & Lip Protection- Do not allow exposure of your skin and lips to sunlight for 8 hours after treatment. In addition, do not expose your skin to either sunlight or sun lamps (regardless of safety claims) within 24 hours of a scheduled treatment. It is advisable to wear protective clothing (hat, gloves) to cover as much of your body as possible after treatment as well as using a sun screen product having a protection factor of at least 15 (only use after treatment).

H. How Long Will The Treatments Last?

May take from six to eight weeks before lesions disappear. Maintenance treatments are usually needed to keep the disease under control.

I. What Are The Problems Associated With Pregnancy Or Breast Feeding?

1. Birth control methods should be employed since the effects of PUVA therapy on the unborn child are not known. If you become pregnant, inform your doctor so that he can determine whether it is necessary for you to temporarily stop therapy.
2. Since it is not known whether Methoxsalen Capsules, USP 10 mg [Soft Gelatin Capsules] passes into mother's milk, it is safer not to breast feed while taking this drug.

J. What Are The Risks Of PUVA Therapy?

1. Premature skin aging may result from prolonged PUVA therapy, especially with those individuals who tan poorly. This problem is similar to excessive exposure to sunlight.
2. There is an increased risk of developing both melanoma and non-melanoma skin cancer. This risk is greater for individuals who fall into the following categories:

a) fair skin that burns rather than tans

b) have had prior treatment with x-rays, grenz rays, or arsenic

c) have had coal tar and UltraViolet B (UVB) treatment.

Even though your doctor will be examining you, you should routinely and completely examine yourself for small growths on your skin or skin sores that will not heal. Immediately report such observations to your doctor.

3. Since studies have shown that animals with unprotected eyes have developed cataracts after PUVA therapy, you should have your eyes examined by an ophthalmologist before starting PUVA therapy, after the first year of therapy and every two years thereafter.

K. What Are The Possible Side Effects?

1. The most common side effects of PUVA therapy are nausea, itching, and redness of the skin. The use of low fat milk or food when ingesting the drug may prevent the nausea.
2. Tenderness or blistering of the skin may occur, but these symptoms can be helped by the use of skin products recommended by your doctor or pharmacist.
3. Less frequent side effects include depression, dizziness, headache, swelling, rash or leg cramps. Important: Contact your doctor if any side effect continues to bother you after 24-48 hours.

Call your doctor for medical advice about adverse effects.

To report SUSPECTED ADVERSE REACTIONS, contact Strides Pharma Inc. at 1-877-244-9825 or go to www.strides.com or FDA at 1-800-FDA-1088 or www.fda.gov/medwatch.

L. What Else Should The Patient Know?

1. Remember to take Methoxsalen Capsules, USP 10 mg [Soft Gelatin Capsules] as directed by your doctor. If you forget to take the drug before your scheduled treatment, be sure to call your doctor to determine what he wishes you to do.
2. Remember that the drug has been prescribed specifically for you and your diagnosed condition. Do not use the drug for any other conditions nor give the drug to others even if they have similar symptoms.
3. If you think that you or anyone else has accidentally taken an overdose, stay out of the sunlight and immediately contact your poison control center, doctor, pharmacist, or nearest hospital emergency room.
4. ALWAYS KEEP THIS DRUG AND ALL OTHER DRUGS OUT OF THE REACH OF CHILDREN.
5. Store at 20° to 25 °C (68° to 77 °F); excursions permitted between 15 °C - 30 °C (59 °F - 86 °F). [See USP Controlled Room Temperature].

Manufactured by:

Strides Pharma Science Ltd.

Bengaluru - 562106, India

Distributed by:

Strides Pharma Inc.

East Brunswick, NJ 08816

Revised: 01/2019

PRINCIPAL DISPLAY PANEL

NDC 64380-752-16

Rx Only

(Methoxsalen Capsules, USP)

10 mg

CAUTION: This new dosage form of methoxsalen exhibits significantly greater bioavailability and earlier photosensitization onset time than previous methoxsalen dosage forms. Each patient should be evaluated by determining the minimum phototoxic dose (MPD) and phototoxic peak time after drug administration prior to onset of photoche-motheraphy with this dosage form.

50 Capsules

50 capsules Container label